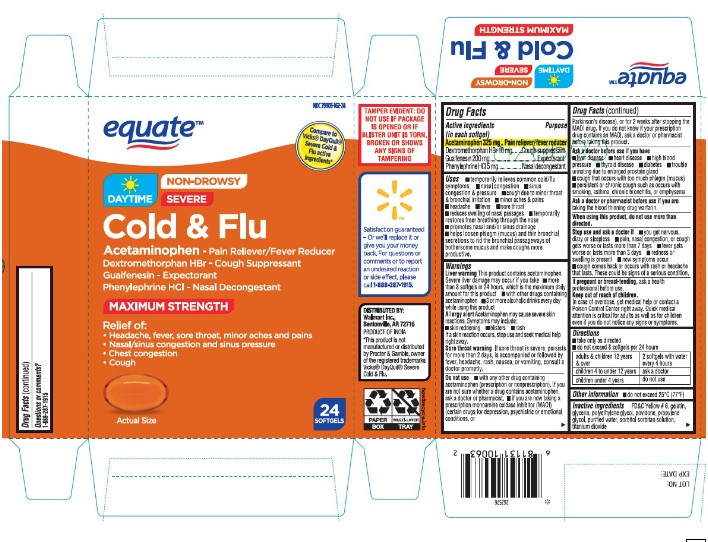 DRUG LABEL: Maximum Strength Non Drowsy Daytime Severe Cold and Flu
NDC: 79903-162 | Form: CAPSULE, LIQUID FILLED
Manufacturer: Wal-Mart Stores Inc
Category: otc | Type: HUMAN OTC DRUG LABEL
Date: 20260126

ACTIVE INGREDIENTS: ACETAMINOPHEN 325 mg/1 1; DEXTROMETHORPHAN HYDROBROMIDE 10 mg/1 1; GUAIFENESIN 200 mg/1 1; PHENYLEPHRINE HYDROCHLORIDE 5 mg/1 1
INACTIVE INGREDIENTS: FD&C YELLOW NO. 6; GELATIN; GLYCERIN; POLYETHYLENE GLYCOL, UNSPECIFIED; POVIDONE; PROPYLENE GLYCOL; SORBITOL; SORBITAN; TITANIUM DIOXIDE

Maximum Strength Non Drowsy Daytime Severe Cold and Flu

Active ingredients (in each caplet)

Acetaminophen
Dextromethorphan HBr 10 mg
Guaifenesin 200 mg
Phenylephrine HCl 5 mg

Purpose

Pain reliever/fever reducer
Cough suppressant
Expectorant
Nasal decongestant

Uses

• for the temporary relief of the following cold/flu symptoms: • minor aches and pains • headache • sore throat • nasal congestion • cough
• helps loosen phlegm (mucus) and thin bronchial secretions to make coughs more productive • temporarily reduces fever

Warnings

Liver warning: This product contains acetaminophen. The maximum daily dose of this product is
10 caplets (3,250 mg acetaminophen) in 24 hours. Severe liver damage may occur if you take:
• more than 4,000 mg of acetaminophen in 24 hours • with other drugs containing acetaminophen
• 3 or more alcoholic drinks every day while using this product

Allergy alert: acetaminophen may cause severe skin reactions. Symptoms may include: • skin reddening • blisters • rash If a skin reaction occurs, stop use and seek medical help right away.

Sore throat warning: If sore throat is severe, persists for more than 2 days, is accompanied or followed by fever, headache, rash, nausea, or vomiting, consult a doctor promptly.

Do not use • with any other drug containing acetaminophen (prescription or nonprescription). If you are not sure whether a drug contains acetaminophen, ask a doctor or pharmacist. • if you
are now taking a prescription monoamine oxidase inhibitor (MAOI) (certain drugs for depression,
psychiatric or emotional conditions, or Parkinson's disease), or for 2 weeks after stopping the
MAOI drug. If you do not know if your prescription drug contains an MAOI, ask a doctor or pharmacist before taking this product. • if you have ever had an allergic reaction to this product or any of its ingredients.

Ask a doctor before use if you have
• liver disease • heart disease • high blood pressure • thyroid disease • diabetes • trouble urinating due to an enlarged prostate gland • persistent or chronic cough such as occurs with smoking, asthma, chronic bronchitis or emphysema • cough that occurs with too much phlegm (mucus)

Ask a doctor or pharmacist before use if you are taking the blood thinning drug warfarin

When using this product do not exceed recommended dosage

Stop use and ask a doctor if • nervousness, dizziness, or sleeplessness occur • pain, nasal congestion or cough gets worse or lasts more than 7 days • fever gets worse or lasts more than 3 days • redness or swelling is present • new symptoms occur • cough comes back or occurs with rash or headache that lasts. These could be signs of a serious condition.

PREGNANCY OR BREAST FEEDING

If pregnant or breast-feeding, ask a health professional before use.

Keep out of reach of children. In case of overdose, get medical help or contact a Poison Control Center right away (1-800-222-1222). Quick medical attention is critical for adults as well as for children even if you do not notice any signs or symptoms

Directions

- do not take more than directed

adults and children 12 years & over | • take 2 caplets every 4 hours • swallow whole; do not crush, chew or dissolve • do not take more than 10 caplets in 24 hours
children under 12 years | ask a doctor

Other information

- do not exceed 25ºC (77ºF)

Inactive Ingredients

FD&C Yellow # 6, gelatin, glycerin, polyethylene glycol, povidone, propylene glycol, purified water, sorbitol sorbitan, titanium dioxide

Questions or comments?

1-888-287-1915

Principal Display Panel

Compare to Vicks® DayQuil® Severe Cold & Flu active ingredients†

Maximum Strength Daytime Non-Drowsy Severe Cold & Flu

ACETAMINOPHEN / PAIN RELIEVER / FEVER REDUCER
DEXTROMETHORPHAN HBr / COUGH SUPPRESSANT
GUAIFENESIN / EXPECTORANT
PHENYLEPHRINE HCI / NASAL DECONGESTANT

Relief of:

- Headache, fever, sore throat, minor aches & pains
- Nasal/sinus congestion & sinus pressure
- Chest congestion
- Cough

24 Softgels